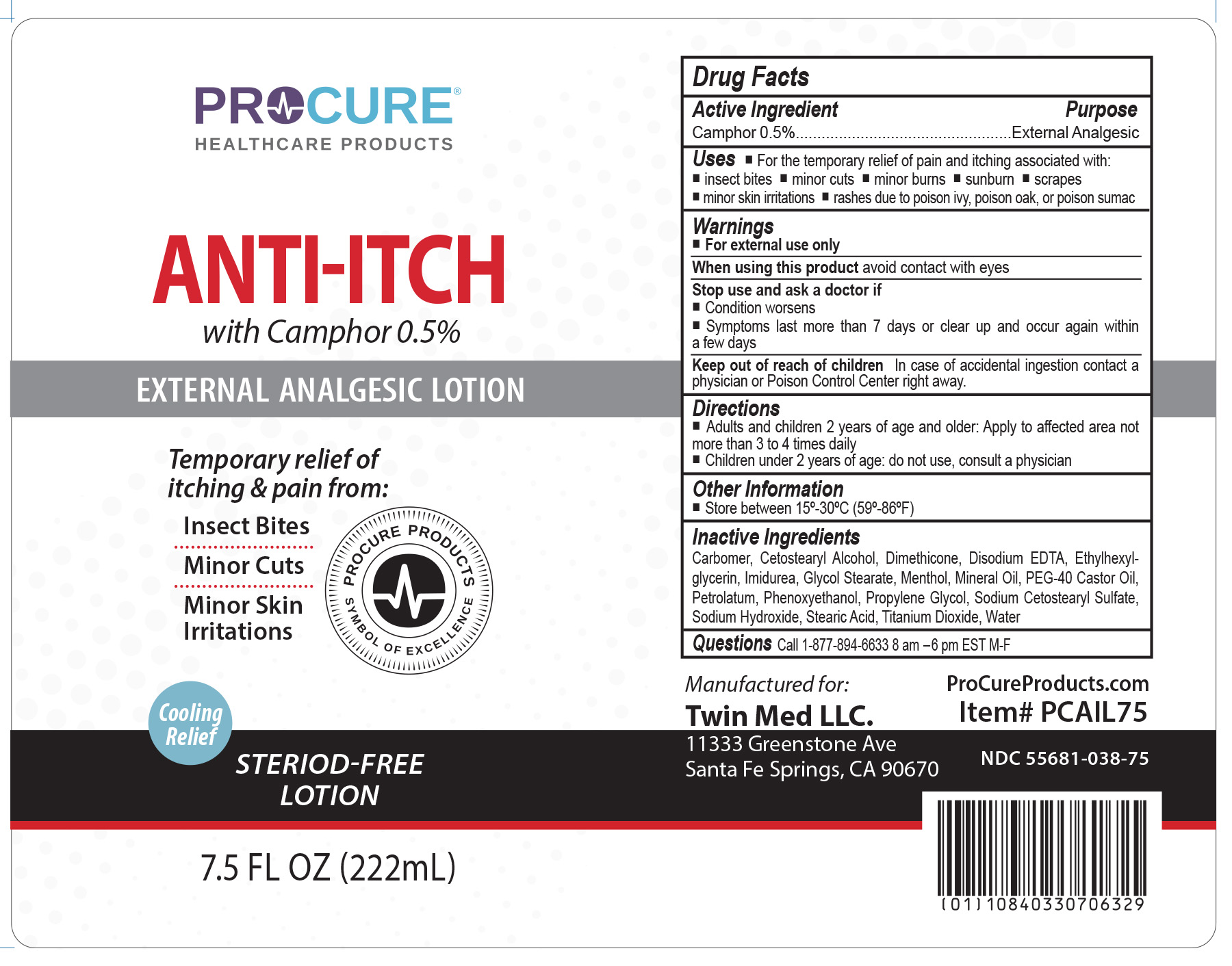 DRUG LABEL: ProCure Anti Itch
NDC: 55681-038 | Form: LOTION
Manufacturer: Twin Med LLC
Category: otc | Type: HUMAN OTC DRUG LABEL
Date: 20250728

ACTIVE INGREDIENTS: CAMPHOR (NATURAL) 0.5 g/100 mL
INACTIVE INGREDIENTS: WATER; CETOSTEARYL ALCOHOL; MENTHOL, UNSPECIFIED FORM; IMIDUREA; GLYCOL STEARATE; MINERAL OIL; ETHYLHEXYLGLYCERIN; PEG-40 CASTOR OIL; CARBOMER HOMOPOLYMER, UNSPECIFIED TYPE; PHENOXYETHANOL; PETROLATUM; SODIUM HYDROXIDE; SODIUM CETOSTEARYL SULFATE; DIMETHICONE, UNSPECIFIED; PROPYLENE GLYCOL; STEARIC ACID; TITANIUM DIOXIDE; EDETATE DISODIUM

Active Ingredient

Camphor 0.5%

Purpose

External Analgesic

Uses

For the temporary relief of pain and itching associated with: nsect bites, minor cuts, minor burns, sunburn, scrapes, minor skin irritations, rashes due to poison ivy, poison oak, or poison sumac

Warnings

For external use only

When using this product avoid contact with the eyes

Stop use and ask a doctor if

- Condition worsens
- Symptoms last more than 7 days or clear up and occur again within a few days

Keep out of reach of children. In case of accidental ingestion contact a physician or Poison Control Center right away.

Directions

- Adults and children 2 years of age and older: Apply to affected area not more than 3 to 4 times daily
- Children under 2 years of age: do not use, consult a physician

Inactive Ingredients

Carbomer, Cetostearyl Alcohol, Dimethicone, Disodium EDTA, Ethylhexylglycerin, Imidurea, Glycol Stearate, Menthol, Mineral Oil, PEG-40 Castor Oil, Petrolatum, Phenoxyethanol, Propylene Glycol, Sodium Cetostearyl Sulfate, Sodium Hydroxide, Stearic Acid, Titanium Dioxide, Water